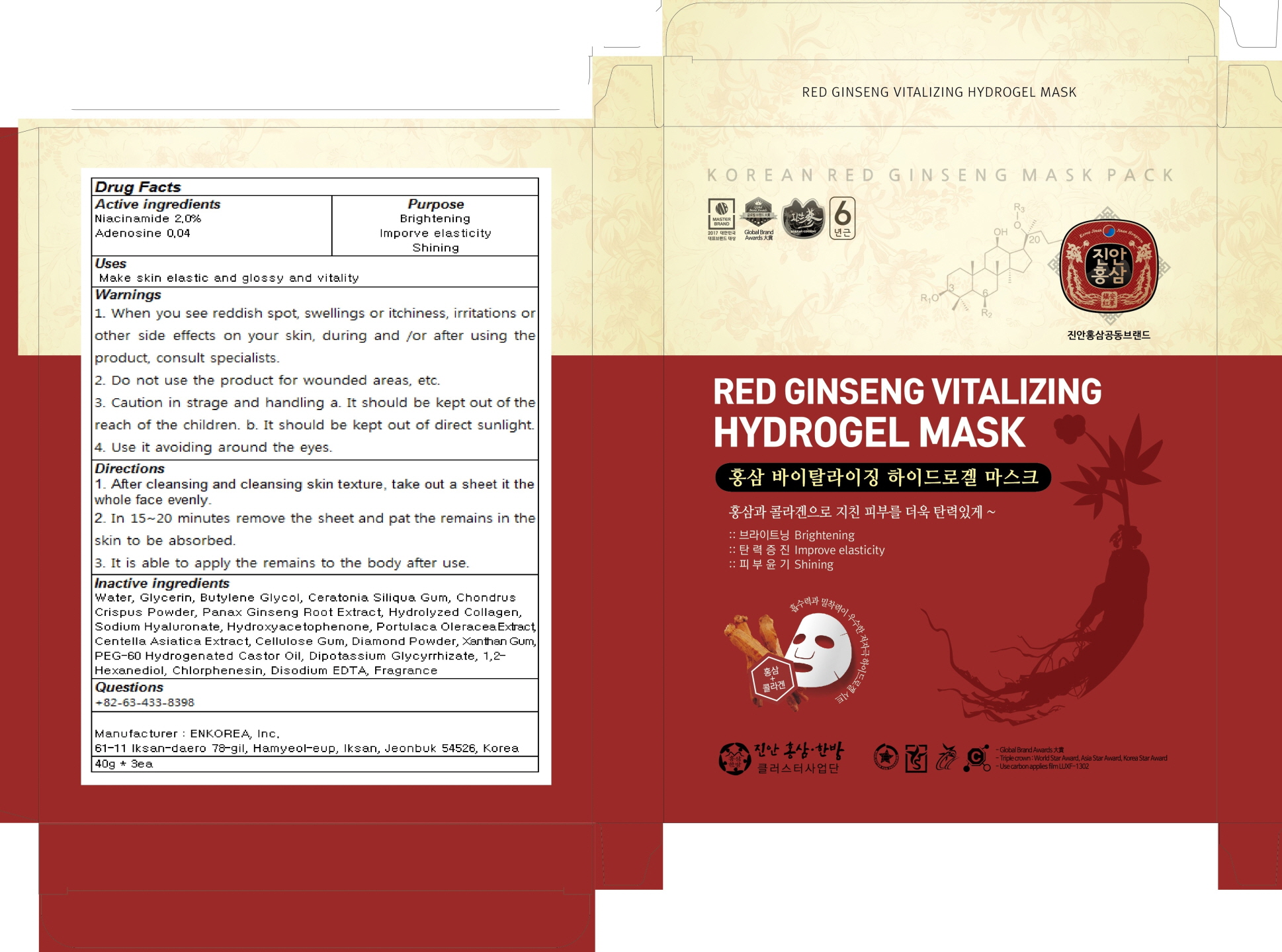 DRUG LABEL: RED GINSENG VITALIZING HYDROG EL MASK
NDC: 71760-010 | Form: PATCH
Manufacturer: ENKOREA, Inc.
Category: otc | Type: HUMAN OTC DRUG LABEL
Date: 20180110

ACTIVE INGREDIENTS: Niacinamide 0.80 g/40 g; Adenosine 0.016 g/40 g
INACTIVE INGREDIENTS: Water; Glycerin

ACTIVE INGREDIENT

Active ingredients: Niacinamide 2.0%, Adenosine 0.04%

INACTIVE INGREDIENT

Inactive Ingredients: Water, Glycerin, Butylene Glycol, Ceratonia Siliqua Gum, Chondrus Crispus Powder, Panax Ginseng Root Extract, Hydrolyzed Collagen, Sodium Hyaluronate, Hydroxyacetophenone, Portulaca Oleracea Extract, Centella Asiatica Extract, Cellulose Gum, Diamond Powder, Xanthan Gum, PEG-60 Hydrogenated Castor Oil, Dipotassium Glycyrrhizate, 1,2-Hexanediol, Chlorphenesin, Disodium EDTA, Fragrance

PURPOSE

Purpose: Brightening, Improve elasticity, Shining

WARNINGS

WARNINGS : 1. When you see reddish spot, swellings or itchiness, irritations or other side effects on your skin, during and /or after using the product, consult specialists. 2. Do not use the product for wounded areas, etc. 3. Caution in strage and handling a. It should be kept out of the reach of the children. b. It should be kept out of direct sunlight. 4. Use it avoiding around the eyes.

KEEP OUT OF REACH OF CHILDREN

It should be kept out of the reach of the children.

USES

USES: Make skin elastic and glossy and vitality

DIRECTIONS

DIRECTIONS: 1. After cleansing and cleansing skin texture, take out a sheet it the whole face evenly. 2. In 15~20 minutes remove the sheet and pat the remains in the skin to be absorbed. 3. It is able to apply the remains to the body after use.

QUESTIONS

Questions: +82-63-433-8398